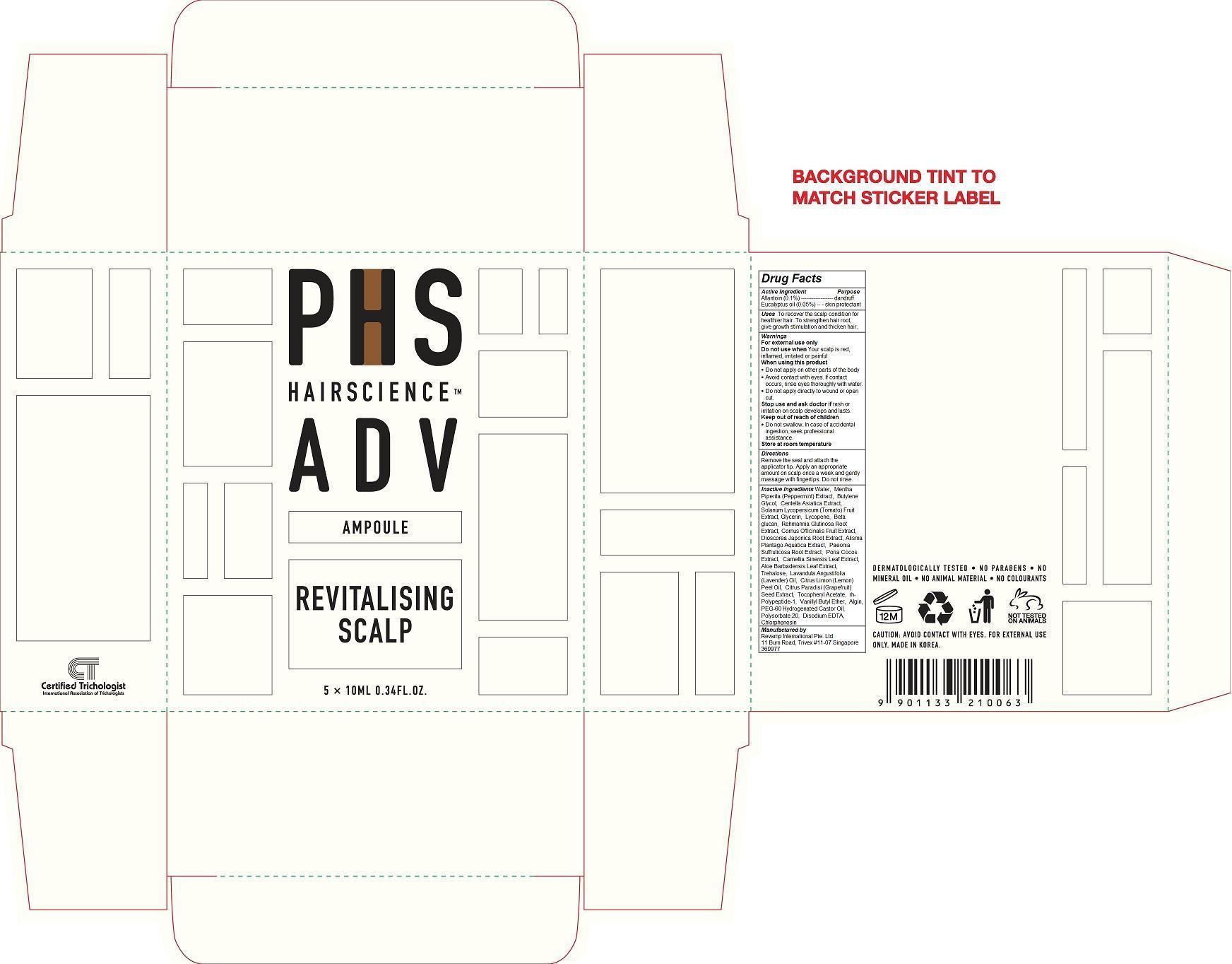 DRUG LABEL: PHS Hair Science Adv Revitalizing Scalp Ampoule
NDC: 69149-103 | Form: LIQUID
Manufacturer: Revamp International Pte. Ltd.
Category: otc | Type: HUMAN OTC DRUG LABEL
Date: 20140917

ACTIVE INGREDIENTS: EUCALYPTUS OIL 0.05 1/10 mL; ALLANTOIN 0.1 1/10 mL
INACTIVE INGREDIENTS: WATER; MENTHA PIPERITA; BUTYLENE GLYCOL; CENTELLA ASIATICA; TOMATO; GLYCERIN; LYCOPENE; REHMANNIA GLUTINOSA ROOT; CORNUS OFFICINALIS FRUIT; DIOSCOREA JAPONICA ROOT; ALISMA PLANTAGO-AQUATICA WHOLE; PAEONIA SUFFRUTICOSA ROOT; FU LING; GREEN TEA LEAF; ALOE VERA LEAF; TREHALOSE; LAVENDER OIL; LEMON OIL; CITRUS PARADISI SEED; .ALPHA.-TOCOPHEROL ACETATE; BASIC FIBROBLAST GROWTH FACTOR (HUMAN); VANILLYL BUTYL ETHER; SODIUM ALGINATE; PEG-60 HYDROGENATED CASTOR OIL; POLYSORBATE 20; EDETATE DISODIUM; CHLORPHENESIN

PHS Hair Science Adv Revitalizing Scalp Ampoule